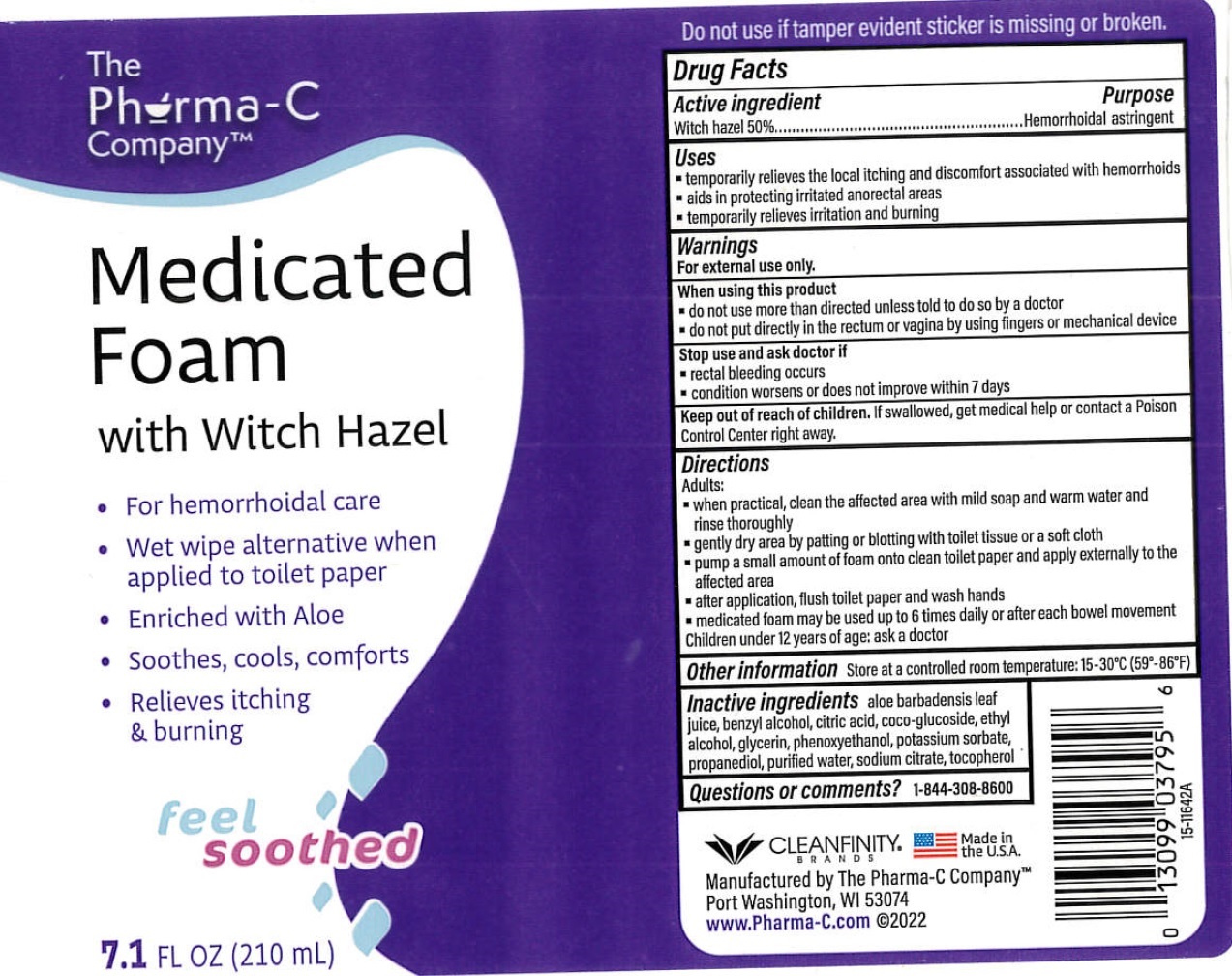 DRUG LABEL: The Pharma C Company Medicated Foam with Witch Hazel
NDC: 55239-358 | Form: LIQUID
Manufacturer: Kleen Test Products Corporation
Category: otc | Type: HUMAN OTC DRUG LABEL
Date: 20231109

ACTIVE INGREDIENTS: WITCH HAZEL 500 mg/1 mL
INACTIVE INGREDIENTS: ALOE VERA LEAF; BENZYL ALCOHOL; CITRIC ACID MONOHYDRATE; COCO GLUCOSIDE; ALCOHOL; GLYCERIN; PHENOXYETHANOL; POTASSIUM SORBATE; PROPANEDIOL; WATER; SODIUM CITRATE; TOCOPHEROL

The Pharma C Company Medicated Foam with Witch Hazel

Active ingredient

Witch hazel 50%

Purpose

Hemorrhoidal astringent

Uses

- temporarily relieves the local itching and discomfort associated with hemorrhoids
- aids in protecting irritated anorectal areas
- temporarily relieves irritation and burning

Warnings

For external use only.

When using this product

- do not use more than directed unless told to do so by a doctor
- do not put directly in the rectum or vagina by using fingers or mechanical device

Stop use and ask doctor if

- rectal bleeding occurs
- condition worsens or does not improve within 7 days

Keep out of reach of children.

If swallowed, get medical help or contact a Poison Control Center right away.

Directions

Adults:

- when practical, clean the affected area with mild soap and warm water and rinse thoroughly
- gently dry area by patting or blotting with toilet tissure or a soft cloth
- pump a small amount of foam onto clean toilet paper and apply externally to the affected area
- after application, flush toilet paper and wash hands
- medicated foam may be used up to 6 times daily or after each bowel movement Children under 12 years of age: ask a doctor

Other information

Store at a controlled room temperature: 15-30°C (59°-86°F)

Inactive ingredients

aloe barbadensis leaf juice, benzyl alcohol, citric acid, coco-glucoside, ethyl alcohol, glycerin, phenoxyethanol, potassium sorbate, propanediol, purified water, sodium citrate, tocopherol

Questions or comments?

1-844-308-8600